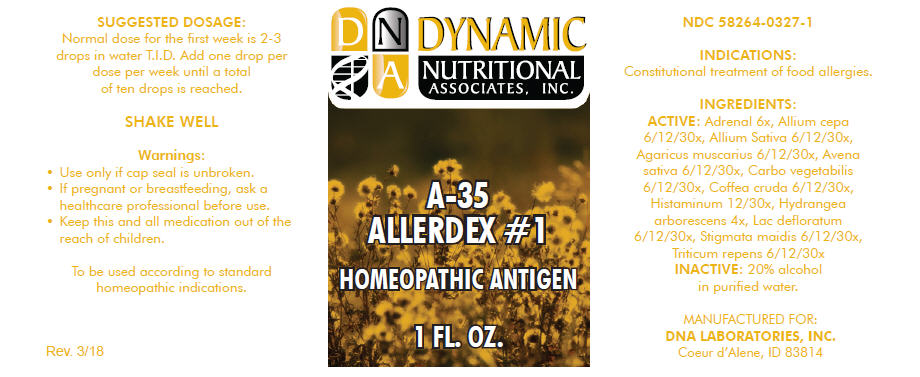 DRUG LABEL: A-35
NDC: 58264-0327 | Form: SOLUTION
Manufacturer: DNA Labs, Inc.
Category: homeopathic | Type: HUMAN OTC DRUG LABEL
Date: 20250109

ACTIVE INGREDIENTS: ACTIVATED CHARCOAL 30 [hp_X]/1 mL; ARABICA COFFEE BEAN 30 [hp_X]/1 mL; HISTAMINE DIHYDROCHLORIDE 30 [hp_X]/1 mL; HYDRANGEA ARBORESCENS ROOT 4 [hp_X]/1 mL; SKIM MILK 30 [hp_X]/1 mL; CORN SILK 30 [hp_X]/1 mL; ELYMUS REPENS WHOLE 30 [hp_X]/1 mL; BOS TAURUS ADRENAL GLAND 6 [hp_X]/1 mL; ONION 30 [hp_X]/1 mL; GARLIC 30 [hp_X]/1 mL; AMANITA MUSCARIA FRUITING BODY 30 [hp_X]/1 mL; AVENA SATIVA FLOWERING TOP 30 [hp_X]/1 mL
INACTIVE INGREDIENTS: ALCOHOL; WATER

A-35

NDC 58264-0327-1

INDICATIONS

PURPOSE

Constitutional treatment of food allergies.

INGREDIENTS

ACTIVE

Adrenal 6x, Allium cepa 6/12/30x, Allium Sativa 6/12/30x, Agaricus muscarius 6/12/30x, Avena sativa 6/12/30x, Carbo vegetabilis 6/12/30x, Coffea cruda 6/12/30x, Histaminum 12/30x, Hydrangea arborescens 4x, Lac defloratum 6/12/30x, Stigmata maidis 6/12/30x, Triticum repens 6/12/30x

INACTIVE

20% alcohol in purified water.

SUGGESTED DOSAGE

Normal dose for the first week is 2-3 drops in water T.I.D. Add one drop per dose per week until a total of ten drops is reached.

SHAKE WELL

Warnings

- Use only if cap seal is unbroken.

PREGNANCY OR BREAST FEEDING

- If pregnant or breastfeeding, ask a healthcare professional before use.

KEEP OUT OF REACH OF CHILDREN

- Keep this and all medication out of the reach of children.

To be used according to standard homeopathic indications.

PRINCIPAL DISPLAY PANEL - 1 FL. OZ. Bottle Label

DYNAMIC
NUTRITIONAL
ASSOCIATES, INC.

A-35
ALLERDEX #1

HOMEOPATHIC ANTIGEN

1 FL. OZ.